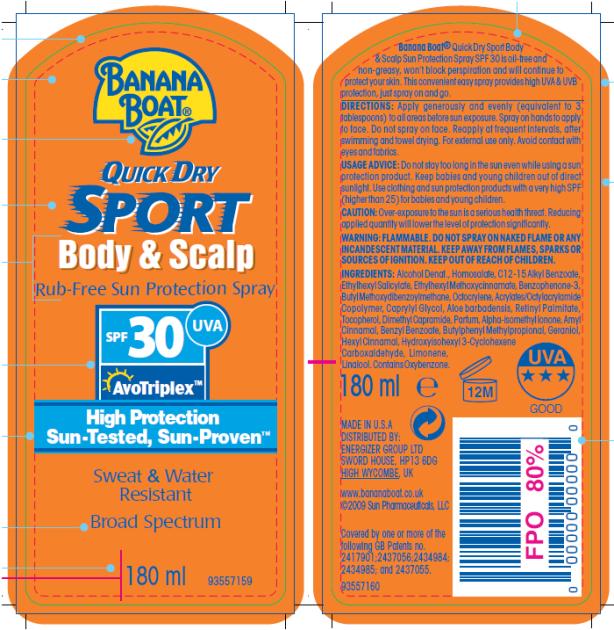 DRUG LABEL: Banana Boat Sport Body and Scalp SPF 30
NDC: 17630-2020 | Form: LOTION
Manufacturer: Accra-Pac, Inc.
Category: otc | Type: HUMAN OTC DRUG LABEL
Date: 20100326

ACTIVE INGREDIENTS: HOMOSALATE 0.0878 mL/1 mL; OCTINOXATE 0.05 mL/1 mL; OCTISALATE 0.05 mL/1 mL; OCTOCRYLENE 0.025 mL/1 mL; OXYBENZONE 0.05 mL/1 mL; AVOBENZONE 0.03 mL/1 mL
INACTIVE INGREDIENTS: C12-15 ALKYL BENZOATE; CAPRYLYL GLYCOL; VITAMIN A PALMITATE; AMYL CINNAMAL; BENZYL BENZOATE; GERANIOL; ALOE VERA LEAF; LIMONENE, DL-; LINALOOL, DL-

Banana Boat Sport Body and Scalp SPF 30

Active Ingredients

Homosalate 0.0878 mL / 1mL

Octinoxate 0.05mL / 1 mL

Octisalate 0.05mL / 1 mL

Octocrylene 0.025mL / 1 mL

Oxybenzone 0.05mL / 1 mL

Avobenzone 0.03 mL / 1mL

DIRECTIONS:

Apply generously and evenly (equivalent to 3 tablespoons) to all areas before sun exposure. Spray on hands to apply to face. Do not spray on face. Reapply at frequent intervals, after swimming and towel drying. For external use only. Avoid contact with eyes and fabrics.

USAGE ADVICE:

Do not stay too long in the sun even while using a sun protection product. Keep babies and young children out of direct sunlight. Use clothing and sun protection products with a very high SPF (higher than 25) for babies and young children.

CAUTION:

Over-exposure to the sun is a serious health threat. Reducing applied quantity will lower the level of protection significantly.

WARNING:

FLAMMABLE. DO NOT SPRAY ON NAKED FLAME OR ANY INCANDESCENT MATERIAL. KEEP AWAY FROM FLAMES, SPARKS OR SOURCES OF IGNITION.

KEEP OUT OF REACH OF CHILDREN.

INGREDIENTS:

Alcohol Denat., Homosalate, C12-15 Alkyl Benzoate, Ethylhexyl Salicylate, Ethylhexyl Methoxycinnamate, Benzophenone-3, Butyl Methoxydibenzoylmethane, Octocrylene, Acrylates/Octylacrylamide Copolymer, Caprylyl Glycol, Aloe barbadensis, Retinyl Palmitate, Tocopherol, Dimethyl Capramide, Parfum, Alpha-isomethyl Ionone, Amyl Cinnamal, Benzyl Benzoate, Butylphenyl Methylpropional, Geraniol, Hexyl Cinnamal, Hydroxyisohexyl 3-Cyclohexene Carboxaldehyde, Limonene, Linalool.
Contains Oxybenzone.

MADE IN U.S.A
DISTRIBUTED BY:
ENERGIZER GROUP LTD
SWORD HOUSE, HP13 6DG
HIGH WYCOMBE, UK
www.bananaboat.co.uk

PRINCIPAL DISPLAY PANEL

BANANA
BOAT®
QUICK DRY
SPORT
Body & Scalp
Rub-Free Sun Protection Spray
SPF 30 UVA
AvoTriplex TM
High Protection
Sun-Tested, Sun-Proven TM
Sweat & Water
Resistant
Broad Spectrum
180 ml